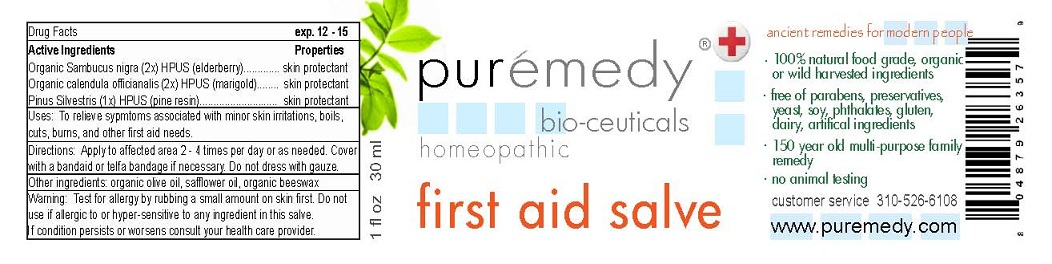 DRUG LABEL: FIRST AID
NDC: 52810-202 | Form: SALVE
Manufacturer: PUREMEDY
Category: homeopathic | Type: HUMAN OTC DRUG LABEL
Date: 20121029

ACTIVE INGREDIENTS: SAMBUCUS NIGRA FLOWER 2 [hp_X]/100 mL; CALENDULA OFFICINALIS FLOWER 2 [hp_X]/100 mL; PINE NEEDLE OIL (PINUS SYLVESTRIS) 1 [hp_X]/100 mL
INACTIVE INGREDIENTS: OLIVE OIL; SAFFLOWER OIL; YELLOW WAX

ACTIVE INGREDIENTS

ORGANIC SAMBUCUS NIGRA (2X) HPUS (ELDERBERRY)

ORGANIC CALENDULA OFFICINALIS (2X) HPUS (MARIGOLD)

PINUS SILVESTRIS (1X) HPUS (PINE RESIN)

PURPOSE

PROPERTIES

SKIN PROTECTANT

SKIN PROTECTANT

SKIN PROTECTANT

INDICATIONS AND USAGE

USES: TO RELIEVE SYMPTOMS ASSOCIATED WITH MINOR SKIN IRRITATIONS, BOILS, CUTS, BURNS, AND OTHER FIRST AID NEEDS.

DOSAGE AND ADMINISTRATION

DIRECTIONS: APPLY TO AFFECTED AREA 2-4 TIMES PER DAY OR AS NEEDED. COVER WITH A BANDAID OR TELFA BANDAGE IF NECESSARY. DO NOT DRESS WITH GAUZA.

INACTIVE INGREDIENT

OTHER INGREDIENTS: ORGANIC OLIVE OIL, SAFFLOWER OIL, ORGANIC BEESWAX.

WARNINGS

WARNING: TEST FOR ALLERGY BY RUBBING A SMALL AMOUNT ON SKIN FIRST. DO NOT USE IF ALLERGIC TO OR HYPER-SENSITIVE TO ANY INGREDIENT IN THIS SALVE. IF CONDITION PERSISTS OR WORSENS CONSULT YOUR HEALTH CARE PROVIDER.

KEEP OUT OF REACH OF CHILDREN.

QUESTIONS

CUSTOMER SERVICE 310-526-6108